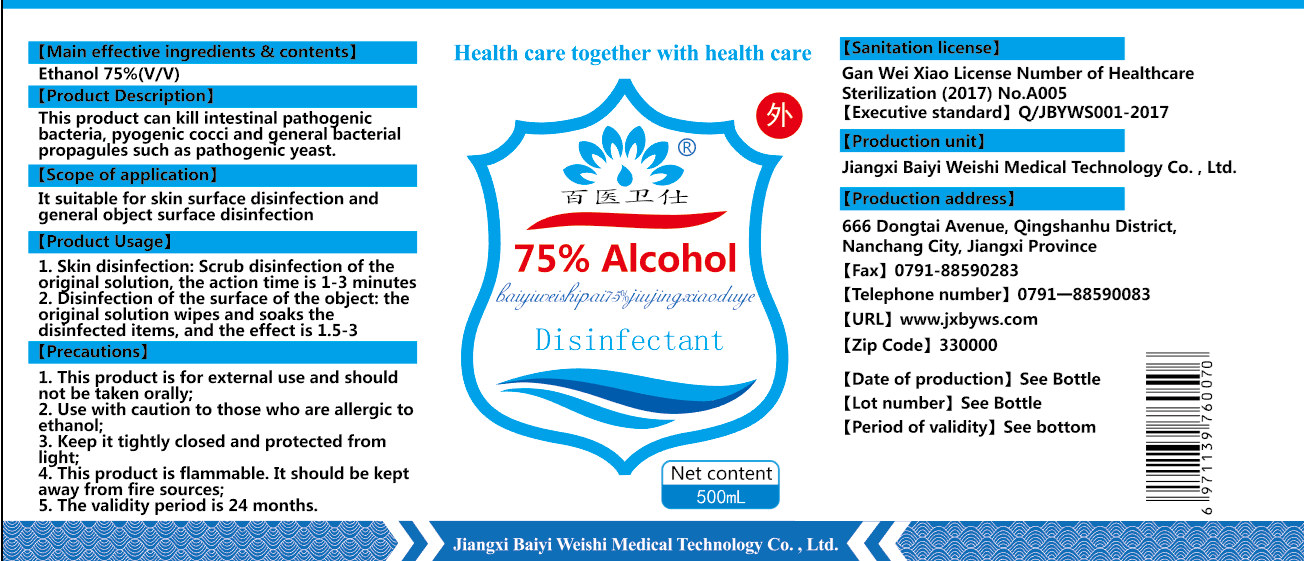 DRUG LABEL: 75% alcohol disinfectant
NDC: 40796-001 | Form: LIQUID
Manufacturer: Jiangxi Baiyi Weishi Medical Technology Co., Ltd.
Category: otc | Type: HUMAN OTC DRUG LABEL
Date: 20200513

ACTIVE INGREDIENTS: ALCOHOL 375 mL/500 mL
INACTIVE INGREDIENTS: WATER

DOSAGE AND ADMINISTRATION

Keep it tightly closed and protected from light

INACTIVE INGREDIENT

Purified water

INDICATIONS AND USAGE

1. Skin disinfection: Scrub disinfection of the original solution, the action time is 1-3 minutes
2. Disinfection of the surface of the object: the original solution wipes and soaks the disinfected items, and the effect is 1.5-3

ACTIVE INGREDIENT

ethanol

keep out of reach of children

PURPOSE

Disinfection
Sterilization

WARNINGS

1. This product is for external use and should not be taken orally;
2. Use with caution to those who are allergic to ethanol;
3. Keep it tightly closed and protected from light; .
4. This product is flammable. It should be kept away from fire sources;
5. The validity period is 24 months.